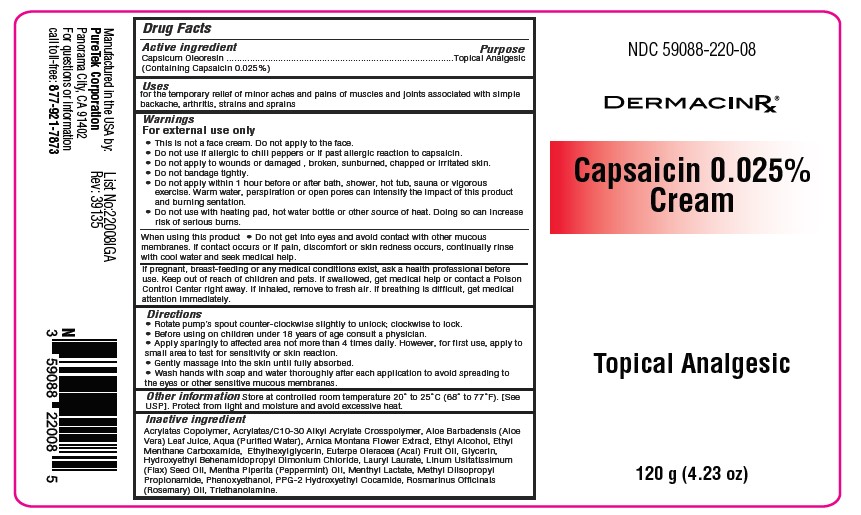 DRUG LABEL: Capsaicin 0.025% Cream
NDC: 59088-220 | Form: CREAM
Manufacturer: Puretek Corporation
Category: otc | Type: HUMAN OTC DRUG LABEL
Date: 20250102

ACTIVE INGREDIENTS: CAPSICUM OLEORESIN 0.025 mg/1 g
INACTIVE INGREDIENTS: ETHYL MENTHANE CARBOXAMIDE; GLYCERIN; MENTHA PIPERITA (PEPPERMINT) OIL; ROSMARINUS OFFICINALIS (ROSEMARY) LEAF OIL; TRIETHANOLAMINE; LAURYL LAURATE; ETHYLHEXYLGLYCERIN; BUTYL ACRYLATE/METHYL METHACRYLATE/METHACRYLIC ACID COPOLYMER (18000 MW); ALCOHOL; MENTHYL LACTATE, (-)-; ALOE BARBADENSIS LEAF JUICE; AQUA; ARNICA MONTANA FLOWER; ACRYLATES/C10-30 ALKYL ACRYLATE CROSSPOLYMER (60000 MPA.S); LINUM USITATISSIMUM (LINSEED) SEED OIL; METHYL DIISOPROPYL PROPIONAMIDE; PPG-2 HYDROXYETHYL COCAMIDE; HYDROXYETHYL BEHENAMIDOPROPYL DIMONIUM CHLORIDE; EUTERPE OLERACEA FRUIT OIL; PHENOXYETHANOL

Capsaicin 0.025% Cream

Active Ingredients:

Capsicum Oleoresin (Containing Capsaicin 0.025%)

Purpose:

Topical Analgesic

Uses

for the temporary relief of minor aches and pains of muscles and joints associated with simple backache, arthritis, strains and sprains

Warnings:

For external use only
• This is not a face cream. Do not apply to the face.
• Do not use if allergic to chili peppers or if past allergic reaction to capsaicin.
• Do not apply to wounds or damaged, broken, sunburned, chapped or irritated skin.
• Do not bandage tightly.
• Do not apply within 1 hour before or after bath, shower, hot tub, sauna or vigorous exercise. Warm water,
perspiration or open pores can intensify the impact of this product and cause a burning sensation.
• Do not use with a heating pad, hot water bottle or other source of heat. Doing so can increase risk of serious
burns.

When using this product

• Do not get into eyes and avoid contact with other mucous membranes. If contact occurs or if pain, discomfort or skin redness occurs, continually rinse with cool water and seek medical help.

KEEP OUT OF REACH OF CHILDREN

If pregnant, breast-feeding or any medical conditions exist, ask a health professional before use. Keep out of reach of children and pets. if swallowed, get medical help or contact a Poison Control Center right away. If inhaled, remove to fresh air. If breathing is difficult, get medical attention immediately.

Directions:

• Rotate pump’s spout counter-clockwise slightly to unlock; clockwise to lock.
• Before using on children under 18 years of age consult a physician.
• Apply sparingly to affected area not more than 4 times daily. However, for first use, apply to small area to test for sensitivity or skin reaction.
• Gently massage into the skin until fully absorbed.
• Wash hands with soap and water thoroughly after each application to avoid spreading to the eyes or other sensitive mucous membranes.

Other information

Store at controlled room temperature 20° to 25°C (68° to 77°F). [See USP]. Protect from light and moisture and avoid excessive heat.

Inactive ingredient

Acrylates Copolymer, Acrylates/C10-30 Alkyl Acrylate Crosspolymer, Aloe Barbadensis (Aloe Vera) Leaf Juice, Aqua (Purified Water), Arnica Montana Flower Extract, Ethyl Alcohol, Ethyl Menthane Carboxamide, Ethylhexylglycerin, Euterpe Oleracea (Acai) Fruit Oil, Glycerin, Hydroxyethyl Behenamidopropyl Dimonium Chloride, Lauryl Laurate, Linum Usitatissimum (Flax) Seed Oil, Mentha Piperita (Peppermint) Oil, Menthyl Lactate, Methyl Diisopropyl Propionamide, Phenoxyethanol, PPG-2 Hydroxyethyl Cocamide, Rosmarinus Officinals (Rosemary) Oil, Triethanolamine.

Label

Manufactured in the USA by:
PureTek Corporation
Panorama City, CA 91402
For questions or information
call toll-free: 877-921-7873